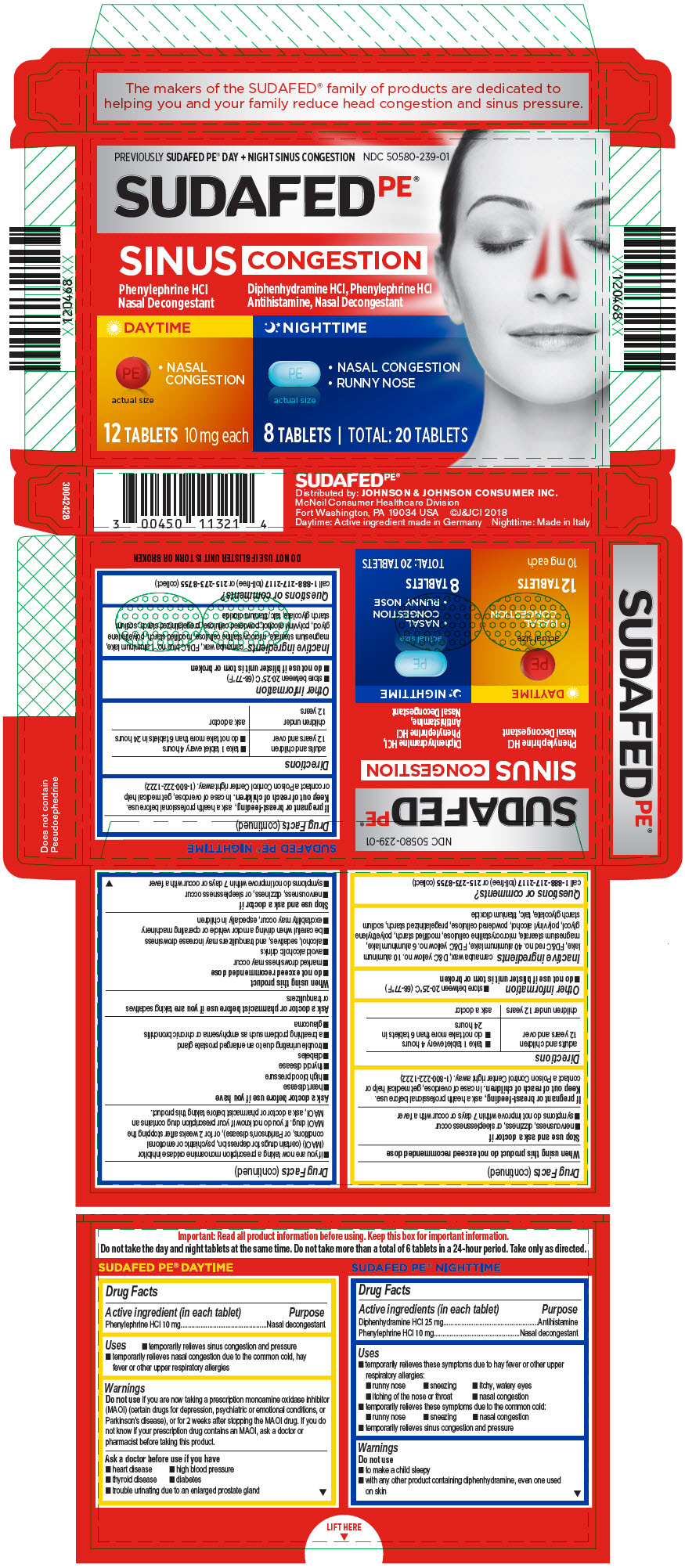 DRUG LABEL: SUDAFED PE SINUS CONGESTION
NDC: 50580-239 | Form: KIT | Route: ORAL
Manufacturer: Kenvue Brands LLC
Category: otc | Type: HUMAN OTC DRUG LABEL
Date: 20241108

ACTIVE INGREDIENTS: PHENYLEPHRINE HYDROCHLORIDE 10 mg/1 1; DIPHENHYDRAMINE HYDROCHLORIDE 25 mg/1 1; PHENYLEPHRINE HYDROCHLORIDE 10 mg/1 1
INACTIVE INGREDIENTS: CARNAUBA WAX; D&C YELLOW NO. 10 ALUMINUM LAKE; FD&C RED NO. 40; FD&C YELLOW NO. 6; ALUMINUM OXIDE; MAGNESIUM STEARATE; MICROCRYSTALLINE CELLULOSE; POLYETHYLENE GLYCOL, UNSPECIFIED; POLYVINYL ALCOHOL, UNSPECIFIED; POWDERED CELLULOSE; SODIUM STARCH GLYCOLATE TYPE A; TALC; TITANIUM DIOXIDE; CARNAUBA WAX; FD&C BLUE NO. 1 ALUMINUM LAKE; MAGNESIUM STEARATE; MICROCRYSTALLINE CELLULOSE; POLYETHYLENE GLYCOL, UNSPECIFIED; POLYVINYL ALCOHOL, UNSPECIFIED; POWDERED CELLULOSE; SODIUM STARCH GLYCOLATE TYPE A; TALC; TITANIUM DIOXIDE

SUDAFED PE SINUS CONGESTION

SUDAFED PE® DAYTIME

Drug Facts

Active ingredient (in each tablet)

Phenylephrine HCl 10 mg

Purpose

Nasal decongestant

Uses

- temporarily relieves sinus congestion and pressure
- temporarily relieves nasal congestion due to the common cold, hay fever or other upper respiratory allergies

Warnings

Do not use if you are now taking a prescription monoamine oxidase inhibitor (MAOI) (certain drugs for depression, psychiatric or emotional conditions, or Parkinson's disease), or for 2 weeks after stopping the MAOI drug. If you do not know if your prescription drug contains an MAOI, ask a doctor or pharmacist before taking this product.

Ask a doctor before use if you have

- heart disease
- high blood pressure
- thyroid disease
- diabetes
- trouble urinating due to an enlarged prostate gland

When using this product do not exceed recommended dose

Stop use and ask a doctor if

- nervousness, dizziness, or sleeplessness occur
- symptoms do not improve within 7 days or occur with a fever

PREGNANCY OR BREAST FEEDING

If pregnant or breast-feeding, ask a health professional before use.

Keep out of reach of children. In case of overdose, get medical help or contact a Poison Control Center right away. (1-800-222-1222)

Directions

adults and children 12 years and over | - take 1 tablet every 4 hours - do not take more than 6 tablets in 24 hours
children under 12 years | ask a doctor

Other information

- store between 20-25°C (68-77°F)
- do not use if blister unit is torn or broken

Inactive ingredients

carnauba wax, D&C yellow no. 10 aluminum lake, FD&C red no. 40 aluminum lake, FD&C yellow no. 6 aluminum lake, magnesium stearate, microcrystalline cellulose, modified starch, polyethylene glycol, polyvinyl alcohol, powdered cellulose, pregelatinized starch, sodium starch glycolate, talc, titanium dioxide

Questions or comments?

call 1-888-217-2117 (toll-free) or 215-273-8755 (collect)

SUDAFED PE® NIGHTTIME

Drug Facts

ACTIVE INGREDIENT

Active ingredients (in each tablet) | Purpose
Diphenhydramine HCl 25 mg | Antihistamine
Phenylephrine HCl 10 mg | Nasal decongestant

Uses

- temporarily relieves these symptoms due to hay fever or other upper respiratory allergies:
  - runny nose
  - sneezing
  - itchy, watery eyes
  - itching of the nose or throat
  - nasal congestion
- temporarily relieves these symptoms due to the common cold:
  - runny nose
  - sneezing
  - nasal congestion
- temporarily relieves sinus congestion and pressure

Warnings

Do not use

- to make a child sleepy
- with any other product containing diphenhydramine, even one used on skin
- if you are now taking a prescription monoamine oxidase inhibitor (MAOI) (certain drugs for depression, psychiatric or emotional conditions, or Parkinson's disease), or for 2 weeks after stopping the MAOI drug. If you do not know if your prescription drug contains an MAOI, ask a doctor or pharmacist before taking this product.

Ask a doctor before use if you have

- heart disease
- high blood pressure
- thyroid disease
- diabetes
- trouble urinating due to an enlarged prostate gland
- a breathing problem such as emphysema or chronic bronchitis
- glaucoma

Ask a doctor or pharmacist before use if you are taking sedatives or tranquilizers

When using this product

- do not exceed recommended dose
- marked drowsiness may occur
- avoid alcoholic drinks
- alcohol, sedatives, and tranquilizers may increase drowsiness
- be careful when driving a motor vehicle or operating machinery
- excitability may occur, especially in children

Stop use and ask a doctor if

- nervousness, dizziness, or sleeplessness occur
- symptoms do not improve within 7 days or occur with a fever

PREGNANCY OR BREAST FEEDING

If pregnant or breast-feeding, ask a health professional before use.

Keep out of reach of children. In case of overdose, get medical help or contact a Poison Control Center right away. (1-800-222-1222)

Directions

adults and children 12 years and over | - take 1 tablet every 4 hours - do not take more than 6 tablets in 24 hours
children under 12 years | ask a doctor

Other information

- store between 20-25°C (68-77°F)
- do not use if blister unit is torn or broken

Inactive ingredients

carnauba wax, FD&C blue no. 1 aluminum lake, magnesium stearate, microcrystalline cellulose, modified starch, polyethylene glycol, polyvinyl alcohol, powdered cellulose, pregelatinized starch, sodium starch glycolate, talc, titanium dioxide

Questions or comments?

call 1-888-217-2117 (toll-free) or 215-273-8755 (collect)

PRINCIPAL DISPLAY PANEL

PREVIOUSLY SUDAFED PE® DAY + NIGHT SINUS CONGESTION
NDC 50580-239-01

SUDAFEDPE®

SINUS CONGESTION

Phenylephrine HCl
Nasal Decongestant

DAYTIME

- NASAL
  CONGESTION

actual size

12 TABLETS 10 mg each

Diphenhydramine HCl, Phenylephrine HCl
Antihistamine, Nasal Decongestant

NIGHTTIME

- NASAL CONGESTION
- RUNNY NOSE

actual size

8 TABLETS | TOTAL: 20 TABLETS